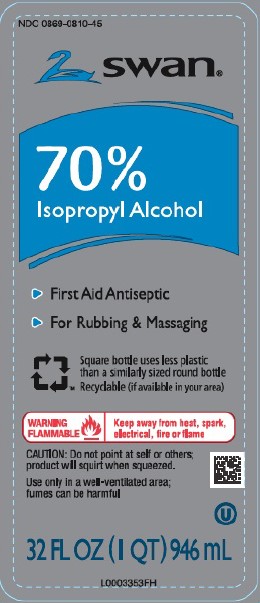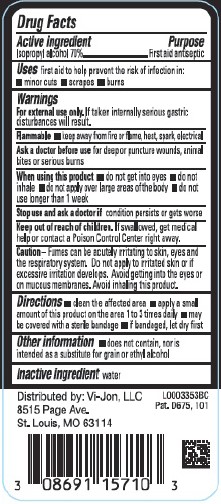 DRUG LABEL: Isopropyl Alcohol
NDC: 0869-0810 | Form: LIQUID
Manufacturer: Vi-Jon, LLC
Category: otc | Type: HUMAN OTC DRUG LABEL
Date: 20250616

ACTIVE INGREDIENTS: ISOPROPYL ALCOHOL 70 mL/100 mL
INACTIVE INGREDIENTS: WATER

Swan 70% Isopropyl Alcohol
810.003/810AA

Active ingredient

Isopropyl alcohol 70%

Purpose

First aid antiseptic

Uses

first aid to help prevent the risk of infection in:

- minor cuts
- scrapes
- burns

Warnings

For external use only.If taken internally serious gastric disturbances will result.

Flammable. Keep away from fire or flame, heat, spark, electrical

Ask a doctor before use

for deep or puncutre wounds, animal bites or serious burns

When using this product

- do not get into eyes
- do not inhale
- do not apply over large areas of the body
- do not use longer than 1 week

Stop use and ask a doctor if

if condition persists or gets worse

Keep out of reach of children.

If swallowed, get medical help or contact a Poison Control Center right away.

Caution

Fumes can be acutely irritating to skin, eyes and the respirtory system. Do not apply to irritated skin of if excessive irritation develops. Avoid getting into the eyes or on mucous membranes. Avoid inhaling this product.

Directions

- clean the affected area
- apply a small amount of this product on the area 1 to 3 times daily
- may be covered with a sterile bandage
- if bandaged, let dry first

other information

- does not contain, nor is intended as a substitute for grain or ethyl alcohol

inactive ingredient

water

Adverse reaction

Distributed by: Vi-Jon, LLC

8515 Page Ave.

St. Louis, MO 63114

Pat. D675, 101

principal display panel

NDC 0869-0810-45

SWAN®

70% Isopropyl Alcohol

- First Aid Antseptic
- For Rubbing & Massaging

Square bottle uses less plastic than a similarly sized bottle

Recyclable (if available in your area)

WARNING FLAMMABLE - Keep away from heat, spark, electrical fire or flame

CAUTION: Do not point at self or other; product will squirt when squeezed.

Use only in a well-ventilated area: fumes can be harmful

32 FL OZ (1 QT) 946 mL